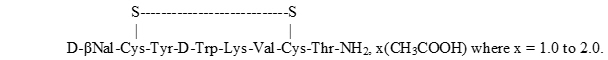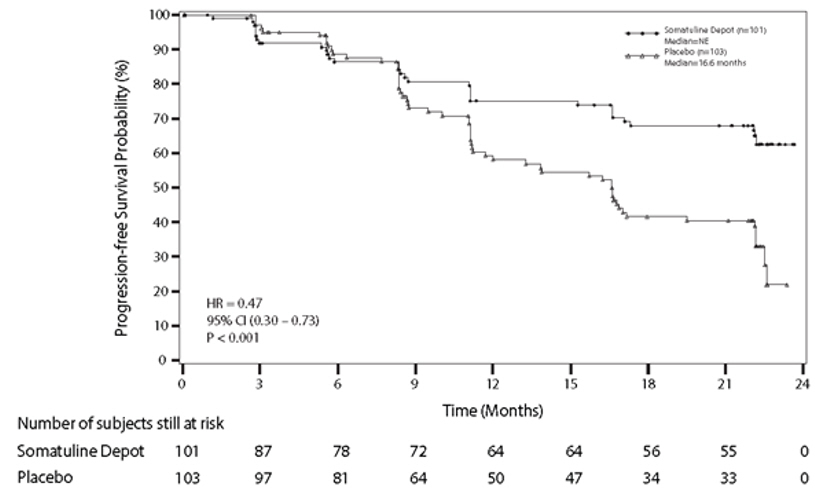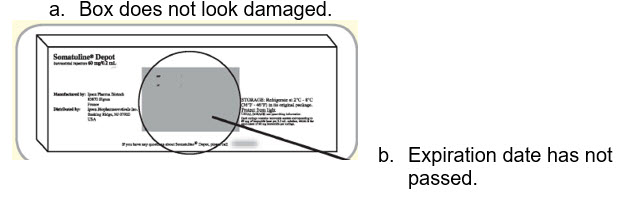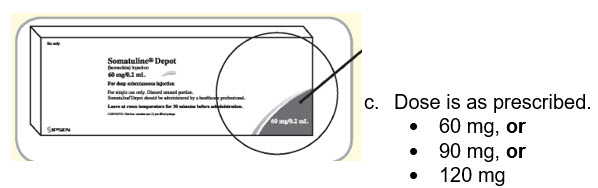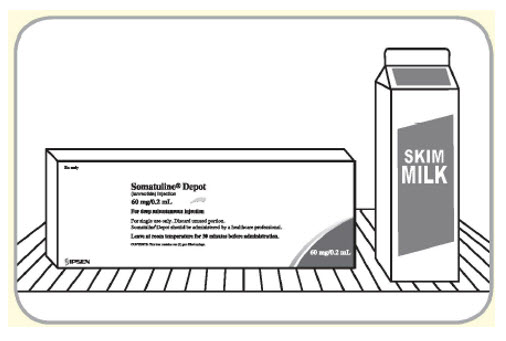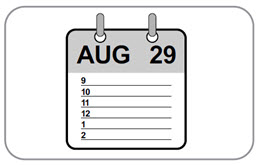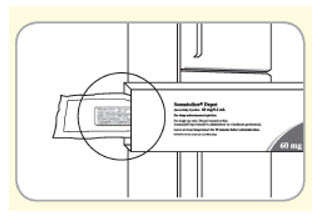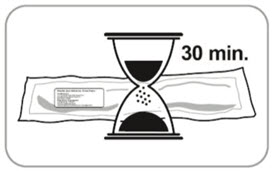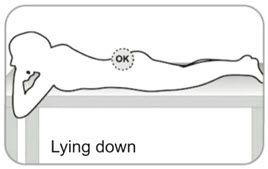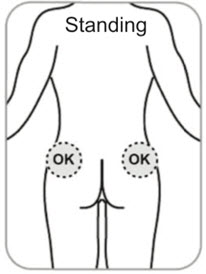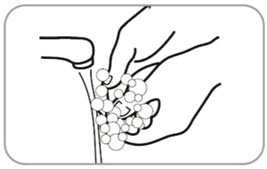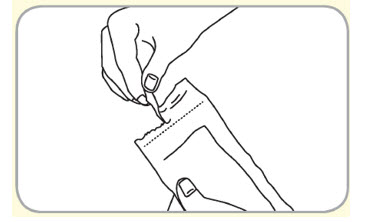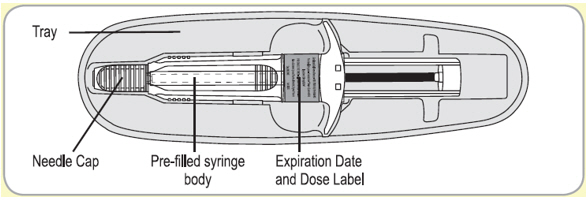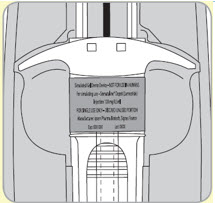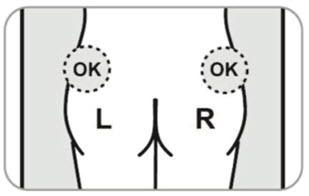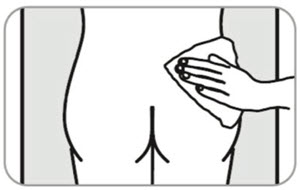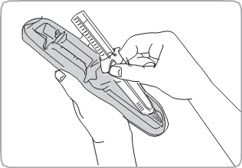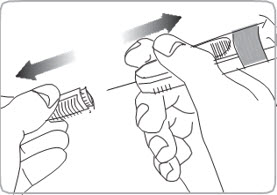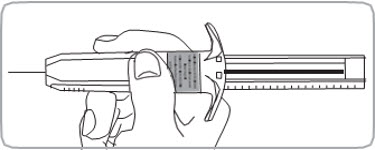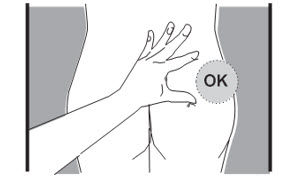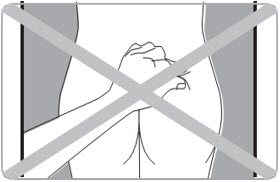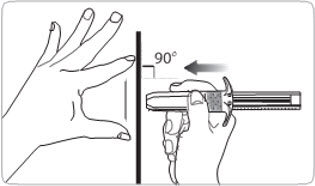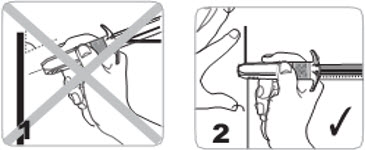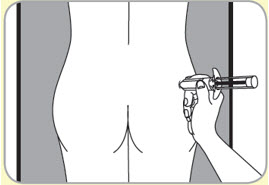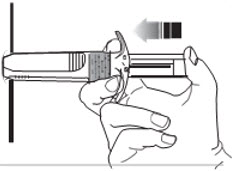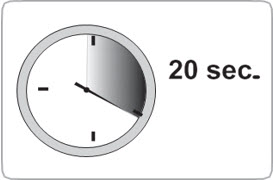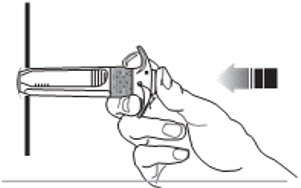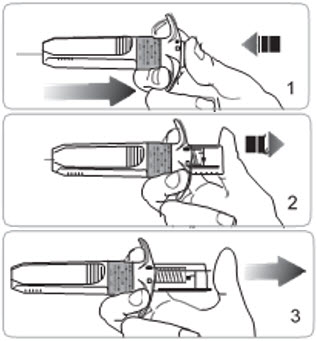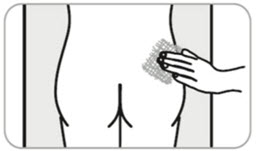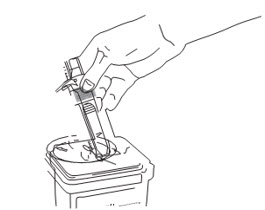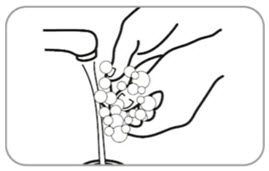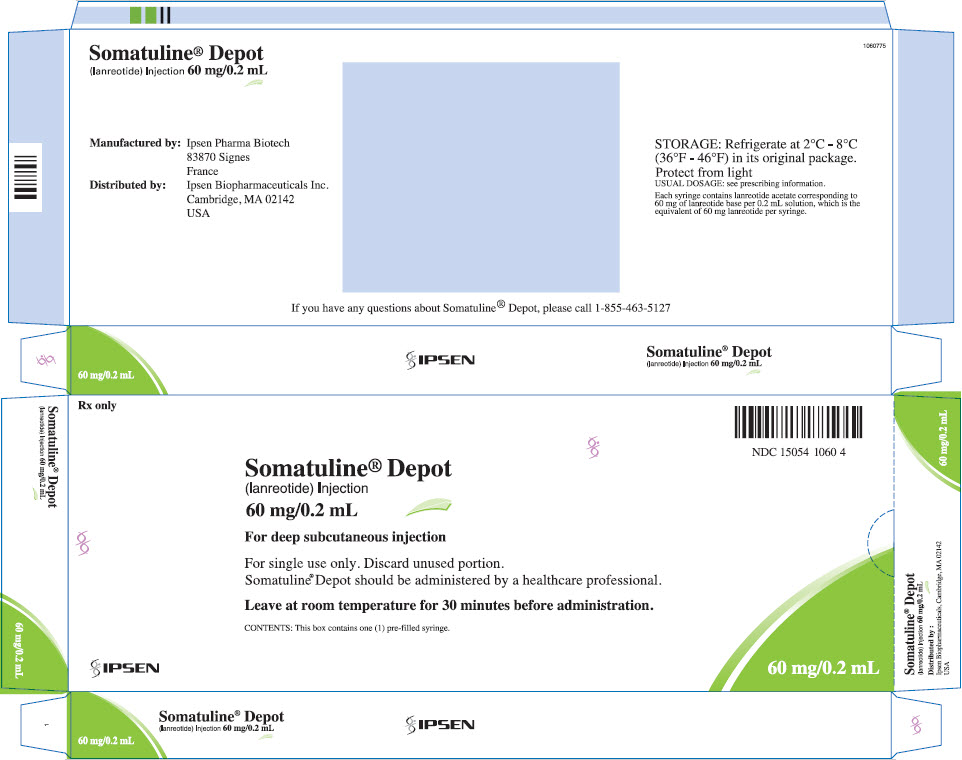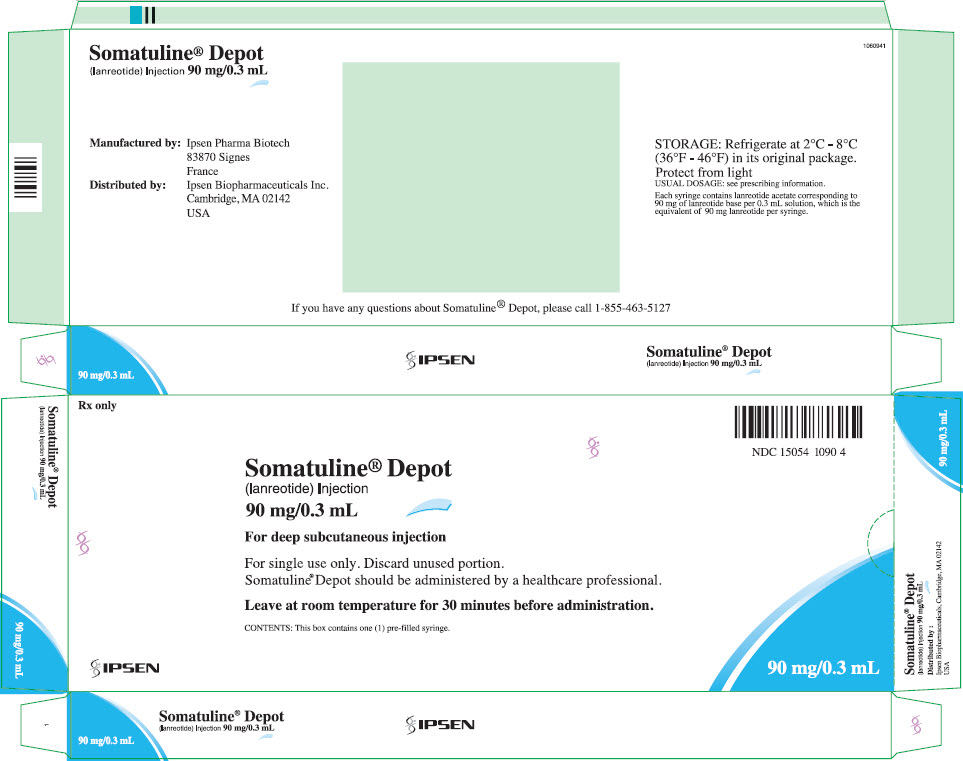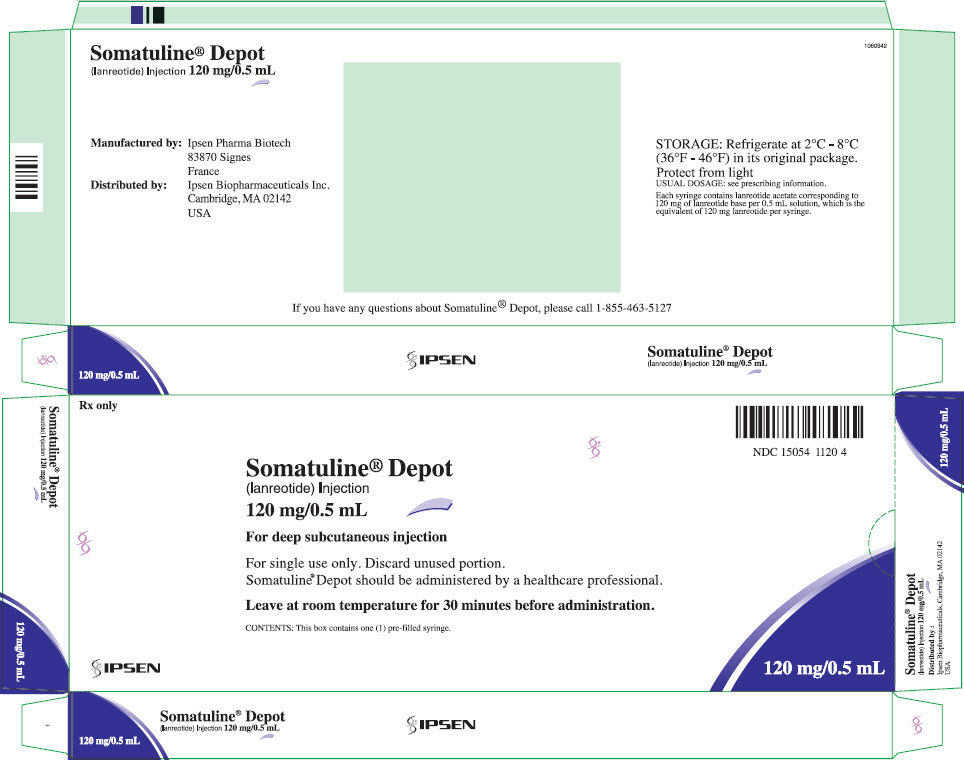 DRUG LABEL: SOMATULINE DEPOT
NDC: 15054-1060 | Form: INJECTION
Manufacturer: Ipsen Biopharmaceuticals, Inc.
Category: prescription | Type: HUMAN PRESCRIPTION DRUG LABEL
Date: 20241011

ACTIVE INGREDIENTS: lanreotide acetate 60 mg/0.2 mL
INACTIVE INGREDIENTS: Water; Acetic Acid

HIGHLIGHTS OF PRESCRIBING INFORMATION

These highlights do not include all the information needed to use SOMATULINE DEPOT safely and effectively. See full prescribing information for SOMATULINE DEPOT.
SOMATULINE® DEPOT (lanreotide) injection, for subcutaneous use
Initial U.S. Approval: 2007

RECENT MAJOR CHANGES

Warnings & Precautions, Steatorrhea and Malabsorption of Dietary Fats (5.6) | 07/2024

1 INDICATIONS AND USAGE

SOMATULINE DEPOT is a somatostatin analog indicated for:

- the long-term treatment of acromegalic patients who have had an inadequate response to or cannot be treated with surgery and/or radiotherapy. (1.1)
- the treatment of adult patients with unresectable, well- or moderately-differentiated, locally advanced or metastatic gastroenteropancreatic neuroendocrine tumors (GEP-NETs) to improve progression-free survival. (1.2)
- the treatment of adults with carcinoid syndrome; when used, it reduces the frequency of short-acting somatostatin analog rescue therapy. (1.3)

2 DOSAGE AND ADMINISTRATION

Administration (2.1):

- For deep subcutaneous injection only.
- Intended for administration by a healthcare provider.
- Administer in the superior external quadrant of the buttock.
- Alternate injection sites.

Recommended Dosage (2.1)

- Acromegaly: 90 mg every 4 weeks for 3 months. Adjust thereafter based on GH and/or IGF-1 levels. See full prescribing information for titration regimen.
- GEP-NETs: 120 mg every 4 weeks.
- Carcinoid Syndrome: 120 mg every 4 weeks. If patients are already being treated with SOMATULINE DEPOT for GEP-NET, do not administer an additional dose for carcinoid syndrome.

Dosage Adjustment:

- See full prescribing information for dosage adjustment in patients with acromegaly and renal or hepatic impairment. (2.3, 2.4)

3 DOSAGE FORMS AND STRENGTHS

Injection: 60 mg/0.2 mL, 90 mg/0.3 mL, and 120 mg/0.5 mL single-dose prefilled syringes (3)

4 CONTRAINDICATIONS

Hypersensitivity to lanreotide. (4)

5 WARNINGS AND PRECAUTIONS

- Cholelithiasis and Complications of Cholelithiasis: Monitor periodically. Discontinue if complications of cholelithiasis are suspected. Gallstones may occur; consider periodic monitoring. (5.1)
- Hyperglycemia and Hypoglycemia: Glucose monitoring is recommended and antidiabetic treatment adjusted accordingly. (5.2, 7.1)
- Cardiovascular Abnormalities: Decrease in heart rate may occur. Use with caution in at-risk patients. (5.3)
- Thyroid Function Abnormalities: Decreases in thyroid function may occur; perform tests where clinically indicated. (5.4)
- Steatorrhea and Malabsorption of Dietary Fats: New onset steatorrhea, stool discoloration, loose stools, abdominal bloating, and weight loss may occur. If new occurrence or worsening of these symptoms are reported, evaluate for potential pancreatic exocrine insufficiency. (5.6)

6 ADVERSE REACTIONS

Most common adverse reactions are:

- Acromegaly (>5%): diarrhea, cholelithiasis, abdominal pain, nausea and injection site reactions. (6.1)
- GEP-NET (>10%): abdominal pain, musculoskeletal pain, vomiting, headache, injection site reaction, hyperglycemia, hypertension, and cholelithiasis. (6.1)
- Carcinoid Syndrome: (≥5% and at least 5% greater than placebo): headache, dizziness and muscle spasm. (6.1)

To report SUSPECTED ADVERSE REACTIONS, contact Ipsen Biopharmaceuticals, Inc. at 1-855-463-5127 or FDA at 1-800-FDA-1088 or www.fda.gov/medwatch

7 DRUG INTERACTIONS

- Cyclosporine: SOMATULINE DEPOT may decrease the absorption of cyclosporine. Dosage adjustment of cyclosporine may be needed. (7.2)
- Bromocriptine: SOMATULINE DEPOT may increase the absorption of bromocriptine. (7.3)
- Bradycardia-Inducing Drugs (e.g., beta-blockers): SOMATULINE DEPOT may decrease heart rate. Dosage adjustment of the coadministered drug may be necessary. (7.3)

8 USE IN SPECIFIC POPULATIONS

Lactation: Advise women not to breastfeed during treatment and for 6 months after the last dose. (8.2)

FULL PRESCRIBING INFORMATION

1 INDICATIONS AND USAGE

1.1 Acromegaly

SOMATULINE DEPOT is indicated for the long-term treatment of acromegalic patients who have had an inadequate response to surgery and/or radiotherapy, or for whom surgery and/or radiotherapy is not an option.

The goal of treatment in acromegaly is to reduce growth hormone (GH) and insulin growth factor-1 (IGF-1) levels to normal.

1.2 Gastroenteropancreatic Neuroendocrine Tumors

SOMATULINE DEPOT is indicated for the treatment of adult patients with unresectable, well or moderately differentiated, locally advanced or metastatic gastroenteropancreatic neuroendocrine tumors (GEP-NETs) to improve progression-free survival.

1.3 Carcinoid Syndrome

SOMATULINE DEPOT is indicated for the treatment of adults with carcinoid syndrome; when used, it reduces the frequency of short-acting somatostatin analog rescue therapy.

2 DOSAGE AND ADMINISTRATION

2.1 Important Administration Instructions

- For deep subcutaneous injection only.
- SOMATULINE DEPOT is intended for administration by a healthcare provider.
- Refer to the Instructions For Use (IFU) for complete administration instructions with illustrations.

Preparation

1. Remove SOMATULINE DEPOT from the refrigerator 30 minutes prior to administration and allow to come to room temperature.
2. Keep pouch sealed until just prior to injection.
3. Product left in its sealed pouch at room temperature (not to exceed 104°F or 40°C) for up to 72 hours may be returned to the refrigerator for continued storage and use at a later time.
4. Prior to administration, inspect the SOMATULINE DEPOT syringe visually for particulate matter and discoloration. Do not administer if particulate matter or discoloration is observed. The content of the prefilled syringe is a semi-solid phase having a gel-like appearance, with viscous characteristics and a color varying from white to pale yellow. The supersaturated solution can also contain micro bubbles that can clear up during injection. These differences are normal and do not interfere with the quality of the product.

Administration

1. Slowly administer for 20 seconds as a deep subcutaneous injection in the superior external quadrant of the buttock.
2. Alternate the injection site between the right and left sides from one injection to the next.

2.2 Recommended Dosage

Acromegaly

The recommended starting dosage of SOMATULINE DEPOT is 90 mg given via the deep subcutaneous route, at 4-week intervals for 3 months.

After 3 months, the dosage may be adjusted as follows:

- GH greater than 1 ng/mL to less than or equal to 2.5 ng/mL, IGF-1 normal, and clinical symptoms controlled: maintain SOMATULINE DEPOT dosage at 90 mg every 4 weeks.
- GH greater than 2.5 ng/mL, IGF-1 elevated, and/or clinical symptoms uncontrolled: increase SOMATULINE DEPOT dosage to 120 mg every 4 weeks.
- GH less than or equal to 1 ng/mL, IGF-1 normal, and clinical symptoms controlled: reduce SOMATULINE DEPOT dosage to 60 mg every 4 weeks.

Thereafter, the dosage should be adjusted according to the response of the patient as judged by a reduction in serum GH and/or IGF-1 levels; and/or changes in symptoms of acromegaly.

Patients who are controlled on SOMATULINE DEPOT 60 or 90 mg may be considered for an extended dosing interval of SOMATULINE DEPOT 120 mg every 6 or 8 weeks. GH and IGF-1 levels should be obtained 6 weeks after this change in dosing regimen to evaluate persistence of patient response.

Continued monitoring of patient response with dosage adjustments for biochemical and clinical symptom control, as necessary, is recommended.

Gastroenteropancreatic Neuroendocrine Tumors (GEP-NETs)

The recommended dosage of SOMATULINE DEPOT is 120 mg administered every 4 weeks by deep subcutaneous injection.

Carcinoid Syndrome

The recommended dosage of SOMATULINE DEPOT is 120 mg administered every 4 weeks by deep subcutaneous injection.

If patients are already being treated with SOMATULINE DEPOT for GEP-NETs, do not administer an additional dose for the treatment of carcinoid syndrome.

2.3 Dosage Adjustment in Renal Impairment

Acromegaly

The recommended starting dosage of SOMATULINE DEPOT in acromegalic patients with moderate or severe renal impairment (creatinine clearance less than 60 mL/min) is 60 mg via the deep subcutaneous route at 4-week intervals for 3 months followed by dosage adjustment [see Dosage and Administration (2.2), Use in Specific Populations (8.6)].

2.4 Dosage Adjustment in Hepatic Impairment

Acromegaly

The recommended starting dosage of SOMATULINE DEPOT in acromegalic patients with moderate or severe hepatic impairment (Child-Pugh Class B or C) is 60 mg via the deep subcutaneous route at 4-week intervals for 3 months followed by dosage adjustment [see Dosage and Administration (2.2), Use in Specific Populations (8.7)].

3 DOSAGE FORMS AND STRENGTHS

Injection: 60 mg/0.2 mL, 90 mg/0.3 mL, and 120 mg/0.5 mL sterile, single-dose, prefilled syringes fitted with an automatic safety system (attached retractable needle and needle guard). The prefilled syringes contain a white to pale yellow, semi-solid formulation.

4 CONTRAINDICATIONS

SOMATULINE DEPOT is contraindicated in patients with history of a hypersensitivity to lanreotide. Allergic reactions (including angioedema and anaphylaxis) have been reported following administration of lanreotide [see Adverse Reactions (6.3)].

5 WARNINGS AND PRECAUTIONS

5.1 Cholelithiasis and Complications of Cholelithiasis

SOMATULINE DEPOT may reduce gallbladder motility and lead to gallstone formation; therefore, patients may need to be monitored periodically [see Adverse Reactions (6.1), Clinical Pharmacology (12.2)]. There have been postmarketing reports of cholelithiasis (gallstones) resulting in complications, including cholecystitis, cholangitis, and pancreatitis, and requiring cholecystectomy in patients taking SOMATULINE DEPOT. If complications of cholelithiasis are suspected, discontinue SOMATULINE DEPOT and treat appropriately.

5.2 Hyperglycemia and Hypoglycemia

Pharmacological studies in animals and humans show that lanreotide, like somatostatin and other somatostatin analogs, inhibits the secretion of insulin and glucagon. Hence, patients treated with SOMATULINE DEPOT may experience hypoglycemia or hyperglycemia. Blood glucose levels should be monitored when lanreotide treatment is initiated, or when the dose is altered, and antidiabetic treatment should be adjusted accordingly [see Adverse Reactions (6.1)].

5.3 Cardiovascular Abnormalities

The most common overall cardiac adverse reactions observed in three pooled SOMATULINE DEPOT cardiac studies in patients with acromegaly were sinus bradycardia (12/217, 5.5%), bradycardia (6/217, 2.8%), and hypertension (12/217, 5.5%) [see Adverse Reactions (6.1)].

In 81 patients with baseline heart rates of 60 beats per minute (bpm) or greater treated with SOMATULINE DEPOT in Study 3, the incidence of heart rate less than 60 bpm was 23% (19/81) as compared to 16% (15/94) of placebo treated patients; 10 patients (12%) had documented heart rates less than 60 bpm on more than one visit. The incidence of documented episodes of heart rate less than 50 bpm as well as the incidence of bradycardia reported as an adverse event was 1% in each treatment group. Initiate appropriate medical management in patients who develop symptomatic bradycardia.

In patients without underlying cardiac disease, SOMATULINE DEPOT may lead to a decrease in heart rate without necessarily reaching the threshold of bradycardia. In patients suffering from cardiac disorders prior to SOMATULINE DEPOT treatment, sinus bradycardia may occur. Care should be taken when initiating treatment with SOMATULINE DEPOT in patients with bradycardia.

5.4 Thyroid Function Abnormalities

Slight decreases in thyroid function have been seen during treatment with lanreotide in acromegalic patients, though clinical hypothyroidism is rare (less than 1%). Thyroid function tests are recommended where clinically indicated.

5.5 Monitoring: Laboratory Tests

Acromegaly: Serum GH and IGF-1 levels are useful markers of the disease and the effectiveness of treatment [see Dosage and Administration (2.2)].

5.6 Steatorrhea and Malabsorption of Dietary Fats

New onset steatorrhea, stool discoloration and loose stools have been reported in patients receiving somatostatin analogs, including SOMATULINE DEPOT. Somatostatin analogs reversibly inhibit secretion of pancreatic enzymes and bile acids, which may result in malabsorption of dietary fats and subsequent symptoms of steatorrhea, loose stools, abdominal bloating, and weight loss. If new occurrence or worsening of these symptoms are reported in patients receiving SOMATULINE DEPOT, evaluate patients for potential pancreatic exocrine insufficiency and manage accordingly.

6 ADVERSE REACTIONS

The following adverse reactions to SOMATULINE DEPOT are discussed in greater detail in other sections of the labeling:

- Cholelithiasis and Complications of Cholelithiasis [see Warnings and Precautions (5.1)]
- Hyperglycemia and Hypoglycemia [see Warnings and Precautions (5.2)]
- Cardiovascular Abnormalities [see Warnings and Precautions (5.3)]
- Thyroid Function Abnormalities [see Warnings and Precautions (5.4)]
- Steatorrhea and Malabsorption of Dietary Fats [see Warnings and Precautions (5.6)]

6.1 Clinical Trials Experience

Because clinical trials are conducted under widely varying conditions, adverse reaction rates observed in the clinical trials of a drug cannot be directly compared to rates in the clinical trials of another drug and may not reflect the rates observed in practice.

Acromegaly

The data described below reflect exposure to SOMATULINE DEPOT in 416 acromegalic patients in seven studies. One study was a fixed-dose pharmacokinetic study. The other six studies were open-label or extension studies, one had a placebo-controlled, run-in period, and another had an active control. The population was mainly Caucasian (329/353, 93%) with a median age of 53 years of age (range 19 to 84 years). Fifty-four subjects (13%) were age 66 to 74 and 18 subjects (4.3%) were 75 years of age and older.

Patients were evenly matched for sex (205 males and 211 females). The median average monthly dose was 91.2 mg (e.g., 90 mg injected via the deep subcutaneous route every 4 weeks) over 385 days with a median cumulative dose of 1290 mg. Of the patients reporting acromegaly, severity at baseline (N=265), serum GH levels were less than 10 ng/mL for 69% (183/265) of the patients and 10 ng/mL or greater for 31% (82/265) of the patients.

The most commonly reported adverse reactions reported by greater than 5% of patients who received SOMATULINE DEPOT (N=416) in the overall pooled safety studies in acromegaly patients were gastrointestinal disorders (diarrhea, abdominal pain, nausea, constipation, flatulence, vomiting, loose stools), cholelithiasis, and injection site reactions.

Tables 1 and 2 present adverse reaction data from clinical studies with SOMATULINE DEPOT in acromegalic patients. The tables include data from a single clinical study and pooled data from seven clinical studies.

Adverse Reactions in Parallel Fixed-Dose Phase of Study 1

The incidence of treatment-emergent adverse reactions for SOMATULINE DEPOT 60, 90, and 120 mg by dose as reported during the first 4 months (fixed-dose phase) of Study 1 [see Clinical Studies (14.1)] are provided in Table 1.

Table 1: Adverse Reactions at an Incidence of Greater than 5% with SOMATULINE DEPOT Overall and Occurring at Higher Rate than Placebo: Placebo-Controlled and Fixed-Dose Phase of Study 1 By Dose
 | Placebo-Controlled Double-Blind Phase Weeks 0 to 4 |  | Fixed-Dose Phase Double-Blind + Single-Blind Weeks 0 to 20
Body System Preferred Term | Placebo (N=25) | SOMATULINE DEPOT Overall (N=83) | SOMATULINE DEPOT 60 mg (N=34) | SOMATULINE DEPOT 90 mg (N=36) | SOMATULINE DEPOT 120 mg (N=37) | SOMATULINE DEPOT Overall (N=107)
 | N (%) | N (%) | N (%) | N (%) | N (%) | N (%)
Gastrointestinal System Disorders | 1 (4%) | 30 (36%) | 12 (35%) | 21 (58%) | 27 (73%) | 60 (56%)
Diarrhea | 0 | 26 (31%) | 9 (26%) | 15 (42%) | 24 (65%) | 48 (45%)
Abdominal pain | 1 (4%) | 6 (7%) | 3 (9%) | 6 (17%) | 7 (19%) | 16 (15%)
Flatulence | 0 | 5 (6%) | 0 (0%) | 3 (8%) | 5 (14%) | 8 (7%)
Application Site Disorders | 0 (0%) | 5 (6%) | 3 (9%) | 4 (11%) | 8 (22%) | 15 (14%)
(Injection site mass/ pain/ reaction/ inflammation)
Liver and Biliary System Disorders | 1 (4%) | 3 (4%) | 9 (26%) | 7 (19%) | 4 (11%) | 20 (19%)
Cholelithiasis | 0 | 2 (2%) | 5 (15%) | 6 (17%) | 3 (8%) | 14 (13%)
Heart Rate & Rhythm Disorders | 0 | 8 (10%) | 7 (21%) | 2 (6%) | 5 (14%) | 14 (13%)
Bradycardia | 0 | 7 (8%) | 6 (18%) | 2 (6%) | 2 (5%) | 10 (9%)
Red Blood Cell Disorders | 0 | 6 (7%) | 2 (6%) | 5 (14%) | 2 (5%) | 9 (8%)
Anemia | 0 | 6 (7%) | 2 (6%) | 5 (14%) | 2 (5%) | 9 (8%)
Metabolic & Nutritional Disorders | 3 (12%) | 13 (16%) | 8 (24%) | 9 (25%) | 4 (11%) | 21 (20%)
Weight decrease | 0 | 7 (8%) | 3 (9%) | 4 (11%) | 2 (5%) | 9 (8%)
A patient is counted only once for each body system and preferred term.
Dictionary = WHOART.

In Study 1, the adverse reactions of diarrhea, abdominal pain, and flatulence increased in incidence with increasing dose of SOMATULINE DEPOT.

Adverse Reactions in Long-Term Clinical Trials

Table 2 provides the most common adverse reactions (greater than 5%) that occurred in 416 acromegalic patients treated with SOMATULINE DEPOT pooled from 7 studies compared to those patients from the 2 efficacy studies (Studies 1 and 2). Patients with elevated GH and IGF-1 levels were either naive to somatostatin analog therapy or had undergone a 3-month washout [see Clinical Studies (14.1)].

Table 2: Adverse Reactions in SOMATULINE DEPOT-Treated Patients at an Incidence Greater than 5% in Overall Group Versus Adverse Reactions Reported in Studies 1 and 2
System Organ Class | Number and Percentage of Patients
System Organ Class | Studies 1 & 2 |  | Overall Pooled Data
System Organ Class | (N=170) |  | (N=416)
System Organ Class | N | % | N | %
Patients with any Adverse Reactions | 157 | 92 | 356 | 86
Gastrointestinal disorders | 121 | 71 | 235 | 57
Diarrhea | 81 | 48 | 155 | 37
Abdominal pain | 34 | 20 | 79 | 19
Nausea | 15 | 9 | 46 | 11
Constipation | 9 | 5 | 33 | 8
Flatulence | 12 | 7 | 30 | 7
Vomiting | 8 | 5 | 28 | 7
Loose stools | 16 | 9 | 23 | 6
Hepatobiliary disorders | 53 | 31 | 99 | 24
Cholelithiasis | 45 | 27 | 85 | 20
General disorders and administration site conditions | 51 | 30 | 91 | 22
(Injection site pain /mass /induration/ nodule/pruritus) | 28 | 17 | 37 | 9
Musculoskeletal and connective tissue disorders | 44 | 26 | 70 | 17
Arthralgia | 17 | 10 | 30 | 7
Nervous system disorders | 34 | 20 | 80 | 19
Headache | 9 | 5 | 30 | 7
Dictionary = MedDRA 7.1

In addition to the adverse reactions listed in Table 2, the following reactions were also seen:

- Sinus bradycardia occurred in 7% (12) of patients in the pooled Study 1 and 2 and in 3% (13) of patients in the overall pooled studies.
- Hypertension occurred in 7% (11) of patients in the pooled Study 1 and 2 and in 5% (20) of patients in the overall pooled studies.
- Anemia occurred in 7% (12) of patients in the pooled Study 1 and 2 and in 3% (14) of patients in the overall pooled studies.

Gastrointestinal Adverse Reactions

In the pooled clinical studies of SOMATULINE DEPOT therapy, a variety of gastrointestinal (GI) reactions occurred, the majority of which were mild to moderate in severity. One percent of acromegalic patients treated with SOMATULINE DEPOT in the pooled clinical studies discontinued treatment because of gastrointestinal reactions.

Pancreatitis was reported in less than 1% of patients.

Gallbladder Adverse Reactions

In clinical studies involving 416 acromegalic patients treated with SOMATULINE DEPOT, cholelithiasis and gallbladder sludge were reported in 20% of the patients. Among 167 acromegalic patients treated with SOMATULINE DEPOT who underwent routine evaluation with gallbladder ultrasound, 17% had gallstones at baseline. New cholelithiasis was reported in 12% of patients. Cholelithiasis may be related to dose or duration of exposure [see Warnings and Precautions (5.1)].

Injection Site Reactions

In the pooled clinical studies, injection site pain (4%) and injection site mass (2%) were the most frequently reported local adverse drug reactions that occurred with the administration of SOMATULINE DEPOT. In a specific analysis, 20 of 413 patients (5%) presented indurations at the injection site. Injection site adverse reactions were more commonly reported soon after the start of treatment and were less commonly reported as treatment continued. Such adverse reactions were usually mild or moderate but did lead to withdrawal from clinical studies in two subjects.

Glucose Metabolism Adverse Reactions

In the clinical studies in acromegalic patients treated with SOMATULINE DEPOT, adverse reactions of dysglycemia (hypoglycemia, hyperglycemia, diabetes) were reported by 14% (47/332) of patients and were considered related to study drug in 7% (24/332) of patients [see Warnings and Precautions (5.2)].

Cardiac Adverse Reactions

In the pooled clinical studies, sinus bradycardia (3%) was the most frequently observed heart rate and rhythm disorder. All other cardiac adverse drug reactions were observed in less than 1% of patients. The relationship of these events to SOMATULINE DEPOT could not be established because many of these patients had underlying cardiac disease [see Warnings and Precautions (5.3)].

A comparative echocardiography study of lanreotide and another somatostatin analog demonstrated no difference in the development of new or worsening valvular regurgitation between the 2 treatments over 1 year. The occurrence of clinically significant mitral regurgitation (i.e., moderate or severe in intensity) or of clinically significant aortic regurgitation (i.e., at least mild in intensity) was low in both groups of patients throughout the study.

Other Adverse Reactions

For the most commonly occurring adverse reactions in the pooled analysis, diarrhea, abdominal pain, and cholelithiasis, there was no apparent trend for increasing incidence with age. GI disorders and renal and urinary disorders were more common in patients with documented hepatic impairment; however, the incidence of cholelithiasis was similar between groups.

Gastroenteropancreatic Neuroendocrine Tumors

The safety of SOMATULINE DEPOT 120 mg for the treatment of patients with gastroenteropancreatic neuroendocrine tumors (GEP-NETs) was evaluated in Study 3, a double-blind, placebo-controlled trial. Patients in Study 3 were randomized to receive SOMATULINE DEPOT (N=101) or placebo (N=103) administered by deep subcutaneous injection once every 4 weeks. The data below reflect exposure to SOMATULINE DEPOT in 101 patients with GEP-NETs, including 87 patients exposed for at least 6 months and 72 patients exposed for at least 1 year (median duration of exposure 22 months). Patients treated with SOMATULINE DEPOT had a median age of 64 years (range 30 to 83 years), 53% were men and 96% were Caucasian. Eighty-one percent of patients (83/101) in the SOMATULINE DEPOT arm and 82% of patients (82/103) in the placebo arm did not have disease progression within 6 months of enrollment and had not received prior therapy for GEP-NETs. The rates of discontinuation due to treatment-emergent adverse reactions were 5% (5/101 patients) in the SOMATULINE DEPOT arm and 3% (3/103 patients) in the placebo arm.

Table 3 compares the adverse reactions reported with an incidence of 5% and greater in patients receiving SOMATULINE DEPOT 120 mg administered every 4 weeks and reported more commonly than placebo.

Table 3: Adverse Reactions Occurring in 5% and Greater of SOMATULINE DEPOT-Treated Patients and at a Higher Rate Than in Placebo-Treated Patients in Study 3
Adverse Reaction | SOMATULINE DEPOT 120 mg N=101 |  | Placebo N=103
Adverse Reaction | Any (%) | Severe [Defined as hazardous to well-being, significant impairment of function or incapacitation] (%) | Any (%) | Severe (%)
Any Adverse Reactions | 88 | 26 | 90 | 31
Abdominal pain [Includes preferred terms of abdominal pain, abdominal pain upper/lower, abdominal discomfort] | 34 [Includes one or more serious adverse events (SAEs) defined as any event that results in death, is life threatening, results in hospitalization or prolongation of hospitalization, results in persistent or significant disability, results in congenital anomaly/birth defect, or may jeopardize the patient and may require medical or surgical intervention to prevent one of the outcomes listed.] | 6 | 24 | 4
Musculoskeletal pain [Includes preferred terms of myalgia, musculoskeletal discomfort, musculoskeletal pain, back pain] | 19 | 2 | 13 | 2
Vomiting | 19 | 2 | 9 | 2
Headache | 16 | 0 | 11 | 1
Injection site reaction [Includes preferred terms of infusion site extravasation, injection site discomfort, injection site granuloma, injections site hematoma, injection site hemorrhage, injection site induration, injection site mass, injections site nodule, injection site pain, injection site pruritus, injection site rash, injection site reaction, injection site swelling] | 15 | 0 | 7 | 0
Hyperglycemia [Includes preferred terms of diabetes mellitus, glucose tolerance impaired, hyperglycemia, type 2 diabetes mellitus] | 14 | 0 | 5 | 0
Hypertension [Includes preferred terms of hypertension, hypertensive crisis] | 14 | 1 | 5 | 0
Cholelithiasis | 14 | 1 | 7 | 0
Dizziness | 9 | 0 | 2 | 0
Depression [Includes preferred terms of depression, depressed mood] | 7 | 0 | 1 | 0
Dyspnea | 6 | 0 | 1 | 0

Carcinoid Syndrome

The safety of SOMATULINE DEPOT 120 mg in patients with histopathologically confirmed neuroendocrine tumors and a history of carcinoid syndrome (flushing and/or diarrhea) was evaluated in Study 4, a double-blind, placebo-controlled trial. Patients were randomized to receive SOMATULINE DEPOT (N=59) or placebo (N=56) administered by deep subcutaneous injection once every 4 weeks. Patients in both arms of Study 4 had access to subcutaneous octreotide as rescue medication for symptom control.

Adverse reactions reported in Study 4 were generally similar to those reported in Study 3 for the GEP-NETs population shown in Table 3 above. Adverse reactions occurring in Study 4 in 5% and greater of SOMATULINE DEPOT-treated patients and occurring at least 5% more than in placebo-treated patients were headache (12% vs 5%, respectively), dizziness (7% vs 0%, respectively), and muscle spasm (5% vs 0%, respectively) by week 16.

6.2 Immunogenicity

As with all peptides, there is potential for immunogenicity. The detection of antibody formation is highly dependent on the sensitivity and specificity of the assay. Additionally, the observed incidence of antibody (including neutralizing antibody) positivity in an assay may be influenced by several factors including assay methodology, sample handling, timing of sample collection, concomitant medications, and underlying disease. For these reasons, comparison of the incidence of antibodies to lanreotide in the studies described below with the incidence of antibodies in other studies or to other products may be misleading.

Laboratory investigations of acromegalic patients treated with SOMATULINE DEPOT in clinical studies show that the percentage of patients with putative antibodies at any time point after treatment is low (less than 1% to 4% of patients in specific studies whose antibodies were tested). The antibodies did not appear to affect the efficacy or safety of SOMATULINE DEPOT.

In Study 3, development of anti-lanreotide antibodies was assessed using a radioimmunoprecipitation assay. In patients with GEP NETs receiving SOMATULINE DEPOT, the incidence of anti-lanreotide antibodies was 4% (3 of 82) at 24 weeks, 10% (7 of 67) at 48 weeks, 11% (6 of 57) at 72 weeks, and 10% (8 of 84) at 96 weeks. Assessment for neutralizing antibodies was not conducted. In Study 4, less than 2% (2 of 108) of the patients treated with SOMATULINE DEPOT developed anti-lanreotide antibodies.

6.3 Postmarketing Experience

The following adverse reactions have been identified during post-approval use of SOMATULINE DEPOT. Because these reactions are reported voluntarily from a population of uncertain size, it is not always possible to reliably estimate their frequency or establish a causal relationship to drug exposure.

Gastrointestinal disorders: pancreatic exocrine insufficiency
Hepatobiliary: steatorrhea; cholecystitis, cholangitis, pancreatitis, which have sometimes required cholecystectomy
Hypersensitivity: angioedema and anaphylaxis
Injection site reactions: injection site abscess

7 DRUG INTERACTIONS

7.1 Insulin and Oral Hypoglycemic Drugs

Lanreotide, like somatostatin and other somatostatin analogs, inhibits the secretion of insulin and glucagon. Therefore, blood glucose levels should be monitored when SOMATULINE DEPOT treatment is initiated or when the dose is altered, and antidiabetic treatment should be adjusted accordingly [see Warnings and Precautions (5.2)].

7.2 Cyclosporine

Concomitant administration of cyclosporine with SOMATULINE DEPOT may decrease the absorption of cyclosporine, and therefore, may necessitate adjustment of cyclosporine dose to maintain therapeutic drug concentrations. [see Clinical Pharmacology (12.3)]

7.3 Bromocriptine

Limited published data indicate that concomitant administration of a somatostatin analog and bromocriptine may increase the absorption of bromocriptine [see Clinical Pharmacology (12.3)].

7.4 Bradycardia-Inducing Drugs

Concomitant administration of bradycardia-inducing drugs (e.g., beta-blockers) may have an additive effect on the reduction of heart rate associated with lanreotide. Dosage adjustments of concomitant drugs may be necessary.

7.5 Drug Metabolism Interactions

The limited published data available indicate that somatostatin analogs may decrease the metabolic clearance of compounds known to be metabolized by cytochrome P450 enzymes, which may be due to the suppression of growth hormone. Since it cannot be excluded that SOMATULINE DEPOT may have this effect, avoid other drugs mainly metabolized by CYP3A4 and which have a low therapeutic index (e.g., quinidine, terfenadine). Drugs metabolized by the liver may be metabolized more slowly during SOMATULINE DEPOT treatment and dose reductions of the concomitantly administered medications should be considered [see Clinical Pharmacology (12.3)].

8 USE IN SPECIFIC POPULATIONS

8.1 Pregnancy

Risk Summary

Limited available data based on postmarketing case reports with SOMATULINE DEPOT use in pregnant women are not sufficient to determine a drug-associated risk of adverse developmental outcomes. In animal reproduction studies, decreased embryo/fetal survival was observed in pregnant rats and rabbits at subcutaneous doses 5- and 2-times the maximum recommended human dose (MRHD) of 120 mg, respectively (see Data).

The estimated background risk of major birth defects and miscarriage for the indicated populations is unknown. All pregnancies have a background risk of birth defect, loss, or other adverse outcomes. In the U.S. general population, the estimated background risk of major birth defects and miscarriage in clinically recognized pregnancies is 2% to 4% and 15% to 20%, respectively.

Data

Animal Data

A reproductive study in pregnant rats given 30 mg/kg of lanreotide by subcutaneous injection every 2 weeks (5 times the human dose, based on body surface area comparisons) resulted in decreased embryo/fetal survival. A study in pregnant rabbits given subcutaneous injections of 0.45 mg/kg/day (2 times the human therapeutic exposures at the maximum recommended dose of 120 mg, based on comparisons of relative body surface area) shows decreased fetal survival and increased fetal skeletal/soft tissue abnormalities.

8.2 Lactation

Risk Summary

There is no information available on the presence of lanreotide in human milk, the effects of the drug on the breastfed infant, or the effects of the drug on milk production. Studies show that lanreotide acetate administered subcutaneously passes into the milk of lactating rats; however, due to specifies-specific differences in lactation physiology, animal data may not reliably predict drug levels in human milk. Because of the potential for serious adverse reactions in breastfed infants from SOMATULINE DEPOT, including effects on glucose metabolism and bradycardia, advise women not to breastfeed during treatment with SOMATULINE DEPOT and for 6 months (6 half-lives) following the last dose.

8.3 Females and Males of Reproductive Potential

Infertility

Females

Based on results from animal studies conducted in female rats, SOMATULINE DEPOT may reduce fertility in females of reproductive potential [see Nonclinical Toxicology (13.1)].

8.4 Pediatric Use

The safety and effectiveness of SOMATULINE DEPOT in pediatric patients have not been established.

8.5 Geriatric Use

No overall differences in safety or effectiveness were observed between elderly patients with acromegaly compared with younger patients and other reported clinical experience has not identified differences in responses between the elderly and younger patients, but greater sensitivity of some older individuals cannot be ruled out. Studies 3 and 4, conducted in patients with neuroendocrine tumors, did not include sufficient numbers of patients aged 65 and over to determine whether they respond differently from younger patients.

Other reported clinical experience has not identified differences in responses between the elderly and younger patients. In general, dose selection for an elderly patient should be cautious, usually starting at the low end of the dosing range, reflecting the greater frequency of decreased hepatic, renal, or cardiac function, and of concomitant disease or other drug therapy.

8.6 Renal Impairment

Acromegaly

Lanreotide has been studied in patients with end-stage renal function on dialysis, but has not been studied in patients with mild, moderate, or severe renal impairment. It is recommended that patients with moderate or severe renal impairment receive a starting dose of lanreotide of 60 mg. Caution should be exercised when considering patients with moderate or severe renal impairment for an extended dosing interval of SOMATULINE DEPOT 120 mg every 6 or 8 weeks [see Dosage and Administration (2.1) and Clinical Pharmacology (12.3)].

Neuroendocrine Tumors (NET) – Gastroenteropancreatic Neuroendocrine Tumors

No effect was observed in total clearance of lanreotide in patients with mild to moderate renal impairment receiving SOMATULINE DEPOT 120 mg. Patients with severe renal impairment were not studied [see Clinical Pharmacology (12.3)].

8.7 Hepatic Impairment

Acromegaly

It is recommended that patients with moderate or severe hepatic impairment receive a starting dose of lanreotide of 60 mg. Caution should be exercised when considering patients with moderate or severe hepatic impairment for an extended dosing interval of SOMATULINE DEPOT 120 mg every 6 or 8 weeks [see Dosage and Administration (2.1) and Clinical Pharmacology (12.3)].

Neuroendocrine Tumors (NET) – Gastroenteropancreatic Neuroendocrine Tumors

SOMATULINE DEPOT has not been studied in patients with hepatic impairment.

11 DESCRIPTION

SOMATULINE DEPOT (lanreotide) Injection 60 mg/0.2 mL, 90 mg/0.3 mL, and 120 mg/0.5 mL is a prolonged-release formulation for deep subcutaneous injection. It contains the drug substance lanreotide acetate, a synthetic octapeptide with a biological activity similar to naturally occurring somatostatin, water for injection and acetic acid (for pH adjustment).

SOMATULINE DEPOT is available as sterile, ready-to-use, single-dose prefilled syringes containing lanreotide acetate supersaturated bulk solution of 24.6% w/w lanreotide base.

Each syringe contains: | SOMATULINE DEPOT 60 mg/0.2 mL | SOMATULINE DEPOT 90 mg/0.3 mL | SOMATULINE DEPOT 120 mg/0.5 mL
Lanreotide acetate | 77.9 mg | 113.6 mg | 149.4 mg
Acetic Acid | q.s. | q.s. | q.s.
Water for injection | 186.6 mg | 272.3 mg | 357.8 mg
Total Weight | 266 mg | 388 mg | 510 mg

Lanreotide acetate is a synthetic cyclical octapeptide analog of the natural hormone, somatostatin. Lanreotide acetate is chemically known as [cyclo S-S]-3-(2-naphthyl)-D-alanyl-L-cysteinyl-L-tyrosyl-D-tryptophyl-L-lysyl-L-valyl-L-cysteinyl-L-threoninamide, acetate salt. Its molecular weight is 1096.34 (base) and its amino acid sequence is:

The SOMATULINE DEPOT in the prefilled syringe is a white to pale yellow, semi-solid formulation.

12 CLINICAL PHARMACOLOGY

12.1 Mechanism of Action

Lanreotide, the active component of SOMATULINE DEPOT is an octapeptide analog of natural somatostatin. The mechanism of action of lanreotide is believed to be similar to that of natural somatostatin.

12.2 Pharmacodynamics

Lanreotide has a high affinity for human somatostatin receptors (SSTR) 2 and 5 and a reduced binding affinity for human SSTR1, 3, and 4. Activity at human SSTR2 and 5 is the primary mechanism believed responsible for GH inhibition. Like somatostatin, lanreotide is an inhibitor of various endocrine, neuroendocrine, exocrine, and paracrine functions.

The primary pharmacodynamic effect of lanreotide is a reduction of GH and/or IGF-1 levels enabling normalization of levels in acromegalic patients [see Clinical Studies (14.1)]. In acromegalic patients, lanreotide reduces GH levels in a dose-dependent way. After a single injection of SOMATULINE DEPOT, plasma GH levels fall rapidly and are maintained for at least 28 days.

In Study 4, patients with carcinoid syndrome treated with SOMATULINE DEPOT 120 mg every 4 weeks had reduced levels of urinary 5-hydroxyindoleacetic acid (5-HIAA) compared with placebo [see Clinical Studies (14.3)].

Lanreotide inhibits the basal secretion of motilin, gastric inhibitory peptide, and pancreatic polypeptide, but has no significant effect on the secretion of secretin. Lanreotide inhibits postprandial secretion of pancreatic polypeptide, gastrin, and cholecystokinin (CCK). In healthy subjects, lanreotide produces a reduction and a delay in postprandial insulin secretion, resulting in transient, mild glucose intolerance.

Lanreotide inhibits meal-stimulated pancreatic secretions, and reduces duodenal bicarbonate and amylase concentrations, and produces a transient reduction in gastric acidity.

Lanreotide has been shown to inhibit gallbladder contractility and bile secretion in healthy subjects [see Warnings and Precautions (5.1)].

In healthy subjects, lanreotide inhibits meal-induced increases in superior mesenteric artery and portal venous blood flow, but has no effect on basal or meal-stimulated renal blood flow. Lanreotide has no effect on renal plasma flow or renal vascular resistance. However, a transient decrease in glomerular filtration rate (GFR) and filtration fraction has been observed after a single injection of lanreotide.

In healthy subjects, non-significant reductions in glucagon levels were seen after lanreotide administration. In diabetic non-acromegalic subjects receiving a continuous infusion (21-day) of lanreotide, serum glucose concentrations were temporarily decreased by 20% to 30% after the start and end of the infusion. Serum glucose concentrations returned to normal levels within 24 hours. A significant decrease in insulin concentrations was recorded between baseline and Day 1 only [see Warnings and Precautions (5.2)].

Lanreotide inhibits the nocturnal increase in thyroid-stimulating hormone (TSH) seen in healthy subjects. Lanreotide reduces prolactin levels in acromegalic patients treated on a long-term basis [see Warnings and Precautions (5.4)].

12.3 Pharmacokinetics

SOMATULINE DEPOT is thought to form a drug depot at the injection site due to the interaction of the formulation with physiological fluids. The most likely mechanism of drug release is a passive diffusion of the precipitated drug from the depot towards the surrounding tissues, followed by the absorption to the bloodstream.

After a single, deep subcutaneous administration, the mean absolute bioavailability of SOMATULINE DEPOT in healthy subjects was 73.4, 69.0, and 78.4% for the 60 mg, 90 mg, and 120 mg doses, respectively. Mean Cmax values ranged from 4.3 to 8.4 ng/mL during the first day. Single-dose linearity was demonstrated with respect to AUC and Cmax, and showed high inter-subject variability. SOMATULINE DEPOT showed sustained release of lanreotide with a half-life of 23 to 30 days. Mean serum concentrations were > 1 ng/mL throughout 28 days at 90 mg and 120 mg and > 0.9 ng/mL at 60 mg.

In studies evaluating excretion, <5% of lanreotide was excreted in urine and less than 0.5% was recovered unchanged in feces, indicative of some biliary excretion.

Acromegaly

In a repeat-dose administration pharmacokinetics (PK) study in acromegalic patients, rapid initial release was seen giving peak levels during the first day after administration. At doses of SOMATULINE DEPOT between 60 and 120 mg, linear pharmacokinetics were observed in acromegalic patients. At steady state, mean Cmax values were 3.8 ± 0.5, 5.7 ± 1.7, and 7.7 ± 2.5 ng/mL, increasing linearly with dose. The mean accumulation ratio index was 2.7, which is in line with the range of values for the half-life of SOMATULINE DEPOT. The steady-state trough serum lanreotide concentrations in patients receiving SOMATULINE DEPOT every 28 days were 1.8 ± 0.3; 2.5 ± 0.9 and 3.8 ± 1.0 ng/mL at 60 mg, 90 mg, and 120 mg doses, respectively. A limited initial burst effect and a low peak-to-trough fluctuation (81% to 108%) of the serum concentration at the plateau were observed.

For the same doses, similar values were obtained in clinical studies after at least four administrations (2.3 ± 0.9, 3.2 ± 1.1, and 4.0 ± 1.4 ng/mL, respectively).

Pharmacokinetic data from studies evaluating extended dosing use of SOMATULINE DEPOT 120 mg demonstrated mean steady-state, Cmin values between 1.6 and 2.3 ng/mL for the 8- and 6-week treatment interval, respectively.

Gastroenteropancreatic Neuroendocrine Tumors

In patients with GEP-NETs treated with SOMATULINE DEPOT 120 mg every 4 weeks, steady state concentrations were reached after 4 to 5 injections and the mean trough serum lanreotide concentrations at steady state ranged from 5.3 to 8.6 ng/mL.

Specific Populations

SOMATULINE DEPOT has not been studied in specific populations. However, the pharmacokinetics of lanreotide in renal impaired, hepatic impaired, and geriatric subjects were evaluated after IV administration of lanreotide immediate release formulation (IRF) at 7 mcg/kg dose.

Geriatric

Studies in healthy elderly subjects showed an 85% increase in half-life and a 65% increase in mean residence time (MRT) of lanreotide compared to those seen in healthy young subjects; however, there was no change in either AUC or Cmax of lanreotide in elderly as compared to healthy young subjects. Age has no effect on clearance of lanreotide based on population PK analysis in patients with GEP-NET which included 122 patients aged 65 to 85 years with neuroendocrine tumors.

Renal Impairment

An approximate 2-fold decrease in total serum clearance of lanreotide, with a consequent 2-fold increase in half-life and AUC was observed. Patients with acromegaly and with moderate to severe renal impairment should begin treatment with SOMATULINE DEPOT 60 mg. Caution should be exercised when considering patients with moderate or severe renal impairment for an extended dosing interval of SOMATULINE DEPOT 120 mg every 6 or 8 weeks.

Mild (CLcr 60-89 mL/min) or moderate (CLcr 30-59 mL/min) renal impairment has no effect on clearance of lanreotide in patients with GEP-NET based on population PK analysis which included 106 patients with mild and 59 patients with moderate renal impairment treated with SOMATULINE DEPOT. GEP-NET patients with severe renal impairment (CLcr < 30 mL/min) were not studied.

Hepatic Impairment

In subjects with moderate to severe hepatic impairment, a 30% reduction in clearance of lanreotide was observed. Patients with acromegaly and with moderate to severe hepatic impairment should begin treatment with SOMATULINE DEPOT 60 mg. Caution should be exercised when considering patients with moderate or severe hepatic impairment for an extended dosing interval of SOMATULINE DEPOT 120 mg every 6 or 8 weeks.

The effect of hepatic impairment on clearance of lanreotide has not been studied in patients with GEP-NET.

13 NONCLINICAL TOXICOLOGY

13.1 Carcinogenesis, Mutagenesis, Impairment of Fertility

Standard lifetime carcinogenicity bioassays were conducted in mice and rats. Mice were given daily subcutaneous doses of lanreotide at 0.5, 1.5, 5, 10, and 30 mg/kg for 104 weeks. Cutaneous and subcutaneous tumors of fibrous connective tissues at the injection sites were observed at the high dose of 30 mg/kg/day. Fibrosarcomas in both genders and malignant fibrous histiocytomas were observed in males at 30 mg/kg/day resulting in exposures 3 times higher than the clinical therapeutic exposure at the maximum therapeutic dose of 120 mg given by monthly subcutaneous injection based on the AUC values. Rats were given daily subcutaneous doses of lanreotide at 0.1, 0.2, and 0.5 mg/kg for 104 weeks. Increased cutaneous and subcutaneous tumors of fibrous connective tissues at the injection sites were observed at the dose of 0.5 mg/kg/day resulting in exposures less than the clinical therapeutic exposure at 120 mg given by monthly subcutaneous injection. The increased incidence of injection site tumors in rodents is likely related to the increased dosing frequency (daily) in animals compared to monthly dosing in humans and therefore may not be clinically relevant.

Lanreotide was not genotoxic in tests for gene mutations in a bacterial mutagenicity (Ames) assay, or mouse lymphoma cell assay with or without metabolic activation. Lanreotide was not genotoxic in tests for the detection of chromosomal aberrations in a human lymphocyte and in vivo mouse micronucleus assay.

In a fertility study conducted with lanreotide in rats, reduced female fecundity was observed at estimated exposure corresponding to approximately 10-fold the plasma exposure at the MRHD of 120 mg. The fertility of male rats was unaffected by the treatment up to an estimated exposure corresponding to approximately 11-fold the plasma exposure at the MRHD of 120 mg.

14 CLINICAL STUDIES

14.1 Acromegaly

The effect of SOMATULINE DEPOT on reducing GH and IGF-levels and control of symptoms in patients with acromegaly was studied in 2 long-term, multiple-dose, randomized, multicenter studies.

Study 1

This 1-year study included a 4-week, double-blind, placebo-controlled phase; a 16-week single-blind, fixed-dose phase; and a 32-week, open-label, dose-titration phase. Patients with active acromegaly, based on biochemical tests and medical history, entered a 12-week washout period if there was previous treatment with a somatostatin analog or a dopaminergic agonist.

Upon entry, patients were randomly allocated to receive a single, deep subcutaneous injection of SOMATULINE DEPOT 60, 90, or 120 mg or placebo. Four weeks later, patients entered a fixed-dose phase where they received 4 injections of SOMATULINE DEPOT followed by a dose-titration phase of 8 injections for a total of 13 injections over 52 weeks (including the placebo phase). Injections were given at 4-week intervals. During the dose-titration phase of the study, the dose was titrated twice (every fourth injection), as needed, according to individual GH and IGF-1 levels.

A total of 108 patients (51 males, 57 females) were enrolled in the initial placebo-controlled phase of the study. Half (54/108) of the patients had never been treated with a somatostatin analog or dopamine agonist, or had stopped treatment for at least 3 months prior to their participation in the study and were required to have a mean GH level greater than 5 ng/mL at their first visit. The other half of the patients had received prior treatment with a somatostatin analog or a dopamine agonist before study entry and at study entry were required to have a mean GH concentration greater than 3 ng/mL and at least a 100% increase in mean GH concentration after washout of medication.

One hundred and seven (107) patients completed the placebo-controlled phase, 105 patients completed the fixed-dose phase, and 99 patients completed the dose-titration phase. Patients not completing withdrew due to adverse events (5) or lack of efficacy (4).

In the double-blind phase of Study 1, a total of 52 (63%) of the 83 lanreotide-treated patients had a greater than 50% decrease in mean GH from baseline to Week 4, including 52%, 44%, and 90% of patients in the 60, 90, and 120 mg groups, respectively, compared to placebo (0%, 0/25). In the fixed-dose phase at Week 16, 72% of all 107 lanreotide-treated patients had a decrease from baseline in mean GH of greater than 50%, including 68% (23/34), 64% (23/36), and 84% (31/37) of patients in the 60, 90, and 120 mg lanreotide treatment groups, respectively. Efficacy achieved in the first 16 weeks was maintained for the duration of the study (see Table 4).

Table 4: Overall Efficacy Results Based on GH and IGF-1 Levels by Treatment Phase in Study 1
 |  | Baseline | Before Titration 1 | Before Titration 2 | Last Value Available [Last Observation Carried Forward]
 |  | N=107 | (16 weeks) N=107 | (32 weeks) N=105 | N=107
GH
≤5.0 ng/mL | Number of Responders (%) | 20 (19%) | 72 (67%) | 76 (72%) | 74 (69%)
≤2.5 ng/mL | Number of Responders (%) | 0 (0%) | 52 (49%) | 59 (56%) | 55 (51%)
≤1.0 ng/mL | Number of Responders (%) | 0 (0%) | 15 (14%) | 18 (17%) | 17 (16%)
Median GH | ng/mL | 10.27 | 2.53 | 2.20 | 2.43
GH Reduction | Median % Reduction | -- | 75.5 | 78.2 | 75.5
IGF-1
Normal [Age-adjusted] | Number of Responders (%) | 9 (8%) | 58 (54%) | 57 (54%) | 62 (58%)
Median IGF-1 | ng/mL | 775.0 | 332.0 [n=105,] | 316.5 [n=102,] | 326.0
IGF-1 Reduction | Median % Reduction | -- | 52.3 | 54.5 | 55.4
IGF-1 Normal + GH ≤2.5 ng/mL | Number of Responders (%) | 0 (0%) | 41 (38%) | 46 (44%) | 44 (41%)

Study 2

This was a 48-week, open-label, uncontrolled, multicenter study that enrolled patients who had an IGF-1 concentration 1.3 times or greater than the upper limit of the normal age-adjusted range. Patients receiving treatment with a somatostatin analog (other than SOMATULINE DEPOT) or a dopaminergic agonist had to attain this IGF-1 concentration after a washout period of up to 3 months.

Patients were initially enrolled in a 4-month, fixed-dose phase where they received 4 deep subcutaneous injections of SOMATULINE DEPOT 90 mg, at 4-week intervals. Patients then entered a dose-titration phase where the dose of SOMATULINE DEPOT was adjusted based on GH and IGF-1 levels at the beginning of the dose-titration phase and, if necessary, again after another 4 injections. Patients titrated up to the maximum dose (120 mg) were not allowed to titrate down again.

A total of 63 patients (38 males, 25 females) entered the fixed-dose phase of the trial and 57 patients completed 48 weeks of treatment. Six patients withdrew due to adverse reactions (3), other reasons (2), or lack of efficacy (1).

After 48 weeks of treatment with SOMATULINE DEPOT at 4-week intervals, 43% (27/63) of the acromegalic patients in this study achieved normal age-adjusted IGF-1 concentrations. Mean IGF-1 concentrations after treatment completion were 1.3 ± 0.7 times the upper limit of normal compared to 2.5 ± 1.1 times the upper limit of normal at baseline.

The reduction in IGF-1 concentrations over time correlated with a corresponding marked decrease in mean GH concentrations. The proportion of patients with mean GH concentrations less than 2.5 ng/mL increased significantly from 35% to 77% after the fixed-dose phase and 85% at the end of the study. At the end of treatment, 24/63 (38%) of patients had both normal IGF-1 concentrations and a GH concentration of less than or equal to 2.5 ng/mL (see Table 5) and 17/63 patients (27%) had both normal IGF-1 concentrations and a GH concentration of less than 1 ng/mL.

Table 5: Overall Efficacy Results Based on GH and IGF-1 Levels by Treatment Phase in Study 2
 |  | Baseline | Before Titration 1 (12 wks) | Before Titration 2 (28 wks) | Last Value Available [Last Observation Carried Forward]
 |  | N=63 | N=63 | N=59 | N=63
IGF-1
Normal [Age-adjusted,] | Number of Responders (%) | 0 (0%) | 17 (27%) | 22 (37%) | 27 (43%)
Median IGF-1 | ng/mL | 689.0 | 382.0 | 334.0 | 317.0
IGF-1 Reduction | Median % Reduction | -- | 41.0 | 51.0 | 50.3
GH
≤5.0 ng/mL | Number of Responders (%) | 40 (64%) | 59 (94%) | 57 (97%) | 62 (98%)
≤2.5 ng/mL | Number of Responders (%) | 21 (33%) | 47 (75%) | 47 (80%) | 54 (86 %)
≤1.0 ng/mL | Number of Responders (%) | 8 (13%) | 19 (30%) | 18 (31%) | 28 (44%)
Median GH | ng/Ml | 3.71 | 1.65 | 1.48 | 1.13
GH Reduction | Median % Reduction | -- | 63.2 | 66.7 | 78.6 [N= 62,]
IGF-1 normal + GH ≤2.5 ng/mL | Number of Responders (%) | 0 (0%) | 14 (22%) | 20 (34%) | 24 (38%)

Examination of age and gender subgroups did not identify differences in response to SOMATULINE DEPOT among these subgroups. The limited number of patients in the different racial subgroups did not raise any concerns regarding efficacy of SOMATULINE DEPOT in these subgroups.

14.2 Gastroenteropancreatic Neuroendocrine Tumors

The efficacy of SOMATULINE DEPOT was established in a multicenter, randomized, double-blind, placebo-controlled trial of 204 patients with unresectable, well or moderately differentiated, metastatic or locally advanced, gastroenteropancreatic neuroendocrine tumors. Patients were required to have non-functioning tumors without hormone-related symptoms. Patients were randomized 1:1 to receive SOMATULINE DEPOT 120 mg (n=101) or placebo (n=103) every 4 weeks until disease progression, unacceptable toxicity, or a maximum of 96 weeks of treatment. Randomization was stratified by the presence or absence of prior therapy and by the presence or absence of disease progression within 6 months of enrollment. The major efficacy outcome measure was progression-free survival (PFS), defined as time to disease progression as assessed by central independent radiological review using the Response Evaluation Criteria in Solid Tumors (RECIST 1.0) or death.

The median patient age was 63 years (range 30 to 92 years) and 95% were Caucasian. Disease progression was present in nine of 204 patients (4.4%) in the 6 months prior to enrollment and 29 patients (14%) received prior chemotherapy. Ninety-one patients (45%) had primary sites of disease in the pancreas, with the remainder originating in the midgut (35%), hindgut (7%), or unknown primary location (13%). The majority (69%) of the study population had grade 1 tumors. Baseline prognostic characteristics were similar between arms with one exception; there were 39% of patients in the SOMATULINE DEPOT arm and 27% of patients in the placebo arm who had hepatic involvement by tumor of greater than 25%.

Patients on the SOMATULINE DEPOT arm had a statistically significant improvement in PFS compared to patients receiving placebo (see Table 6 and Figure 1).

Table 6: Efficacy Results in Study 3
 | SOMATULINE DEPOT | Placebo
 | n=101 | n=103
Number of Events (%) | 32 (31.7%) | 60 (58.3%)
Median PFS (months)(95% CI) | NE [NE = not reached at 22 months] (NE, NE) | 16.6 (11.2, 22.1)
HR (95% CI) | 0.47 (0.30, 0.73) [Hazard Ratio is derived from a Cox stratified proportional hazards model]
Log-rank p-value | <0.001

Figure 1: Kaplan-Meier Curves of Progression-Free Survival

14.3 Carcinoid Syndrome

Study 4 was a multicenter, randomized, 16-week, double-blind, placebo-controlled trial in 115 patients with histopathologically-confirmed neuroendocrine tumors and a history of carcinoid syndrome (flushing and/or diarrhea) who were treatment naïve or stable on another somatostatin analog and who were randomized 1:1 to receive SOMATULINE DEPOT 120 mg (n=59) or placebo (n=56) by deep subcutaneous injection every 4 weeks. Patients were instructed to self-administer a short-acting somatostatin analog (octreotide) as rescue medication as needed for symptom control. The use of rescue therapy and the severity and frequency of diarrhea and flushing symptoms were reported daily in electronic patient diaries. During the 16 week double-blind phase, the primary efficacy outcome measure was the percentage of days in which patients administered at least one injection of rescue medication for symptom control. Average daily frequencies of diarrhea and flushing events were assessed secondarily.

The patient population had a mean age of 59 years (range 27 to 85 years), 58% were female and 77% were Caucasian. Patients in the SOMATULINE DEPOT arm experienced 15% fewer days on rescue medication compared to patients in the placebo arm (34% vs. 49% of days, respectively; p=0.02). The average daily frequencies of diarrhea and flushing events in patients treated with SOMATULINE DEPOT (and rescue medication) were numerically lower relative to patients treated with placebo (and rescue medication), but were not statistically significantly different via hierarchical testing.

16 HOW SUPPLIED/STORAGE AND HANDLING

SOMATULINE DEPOT is supplied in strengths of 60 mg/0.2 mL, 90 mg/0.3 mL, and 120 mg/0.5 mL as a white to pale yellow, semi-solid formulation in a single, sterile, prefilled, ready-to-use, polypropylene syringe fitted with an automatic safety system, a bromobutyl rubber plunger stopper and a 20 mm attached needle covered by a plastic cap.

Each prefilled syringe is placed in a plastic tray, sealed in a laminated pouch and packed in a carton.

NDC 15054-1060-4 | 60 mg/0.2 mL, sterile, prefilled syringe
NDC 15054-1090-4 | 90 mg/0.3 mL, sterile, prefilled syringe
NDC 15054-1120-4 | 120 mg/0.5 mL, sterile, prefilled syringe

Storage and Handling

Store SOMATULINE DEPOT in the refrigerator at 2°C to 8°C (36°F to 46°F).

Protect from light.

Store in the original package.

17 PATIENT COUNSELING INFORMATION

Advise the patient to read the FDA-approved patient labeling (Patient Information).

Hypersensitivity Reactions

Advise patients to immediately contact their healthcare provider if they experience serious hypersensitivity reactions, such as angioedema or anaphylaxis [see Contraindications (4)].

Cholelithiasis and Complications of Cholelithiasis

Advise patients to contact their healthcare provider if they experience signs or symptoms of gallstones (cholelithiasis) or complications of gallstones (e.g., cholecystitis, cholangitis, or pancreatitis) [see Warnings and Precautions (5.1)].

Hyperglycemia and Hypoglycemia

Advise patients to immediately contact their healthcare provider if they experience signs or symptoms of hyper- or hypoglycemia [see Warnings and Precautions (5.2)].

Cardiovascular Abnormalities

Advise patients to immediately contact their healthcare provider if they experience bradycardia [see Warnings and Precautions (5.3)].

Thyroid Function Abnormalities

Advise patients to contact their healthcare provider if they experience signs or symptoms of hypothyroidism [see Warnings and Precautions (5.4)].

Laboratory Tests

Advise patients with acromegaly that response to SOMATULINE DEPOT should be monitored by periodic measurements of GH and IGF-1 levels, with a goal of decreasing these levels to the normal range [see Dosage and Administration (2.2)].

Steatorrhea and Malabsorption of Dietary Fats

Advise patients to contact their healthcare provider if they experience new or worsening symptoms of steatorrhea, stool discoloration, loose stools, abdominal bloating, and weight loss [see Warnings and Precautions (5.6)].

Lactation

Advise women not to breastfeed during treatment with SOMATULINE DEPOT and for 6 months after the last dose [see Use in Specific Populations (8.2)].

Infertility

Advise females of reproductive potential of the potential for reduced fertility from SOMATULINE DEPOT [see Use in Specific Populations (8.3)].

Manufactured by:
Ipsen Pharma Biotech
83870 Signes, France

Distributed by:
Ipsen Biopharmaceuticals, Inc.
Cambridge, MA, 02142 USA

Patient Information
SOMATULINE® DEPOT (So-mah-tu-leen Dee-Poh)
(lanreotide) injection

Read this Patient Information before you receive your first SOMATULINE DEPOT injection and before each injection. There may be new information. This information does not take the place of talking with your healthcare provider about your medical condition or your treatment.

What is SOMATULINE DEPOT?

SOMATULINE DEPOT is a prescription medicine used for:

- the long-term treatment of people with acromegaly when:
  - surgery or radiotherapy have not worked well enough or
  - they are not able to have surgery or radiotherapy
- the treatment of adults with a type of cancer known as neuroendocrine tumors, from the gastrointestinal tract or the pancreas (GEP-NETs) that has spread or cannot be removed by surgery
- the treatment of adults with carcinoid syndrome to reduce the need for the use of short-acting somatostatin medicine

It is not known if SOMATULINE DEPOT is safe and effective in children.

Who should not receive SOMATULINE DEPOT?

Do not receive SOMATULINE DEPOT if you are allergic to lanreotide.

What should I tell my healthcare provider before receiving SOMATULINE DEPOT?

Before you receive SOMATULINE DEPOT, tell your healthcare provider about all of your medical conditions, including if you:

- have gallbladder problems
- have diabetes
- have heart problems
- have thyroid problems
- have kidney problems
- have liver problems
- are pregnant or plan to become pregnant. It is not known if SOMATULINE DEPOT will harm your unborn baby
- are breastfeeding or plan to breastfeed. It is not known if SOMATULINE DEPOT passes into your breast milk. You should not breastfeed if you receive SOMATULINE DEPOT and for 6 months after your last dose of SOMATULINE DEPOT
- are a female who can become pregnant. SOMATULINE DEPOT may affect fertility in females and may affect your ability to become pregnant. Talk to your healthcare provider if this is a concern for you

Tell your healthcare provider about all the medicines you take, including prescription and over-the-counter medicines, vitamins, and herbal supplements. SOMATULINE DEPOT and other medicines may affect each other, causing side effects. SOMATULINE DEPOT may affect the way other medicines work, and other medicines may affect how SOMATULINE DEPOT works. Your dose of SOMATULINE DEPOT or your other medicines may need to be changed.

Especially tell your healthcare provider if you take:

- insulin or other diabetes medicines
- cyclosporine (Gengraf, Neoral, or Sandimmune)
- medicines that lower your heart rate such as beta blockers

How will I receive SOMATULINE DEPOT?

- You will receive a SOMATULINE DEPOT injection every 4 weeks in your healthcare provider's office
- Your healthcare provider may change your dose of SOMATULINE DEPOT or the length of time between your injections. Your healthcare provider will tell you how long you need to receive SOMATULINE DEPOT
- SOMATULINE DEPOT is injected deep under the skin of the upper outer area of your buttock. Your injection site should change (alternate) between your right and left buttock from one injection of SOMATULINE DEPOT to the next
- During your treatment with SOMATULINE DEPOT for acromegaly, your healthcare provider may do certain blood tests to see if SOMATULINE DEPOT is working

What should I avoid while receiving SOMATULINE DEPOT?

SOMATULINE DEPOT can cause dizziness. If you have dizziness, do not drive a car or operate machinery.

What are the possible side effects of SOMATULINE DEPOT?

SOMATULINE DEPOT may cause serious side effects, including:

- Gallstones (cholelithiasis) and complications that can happen if you have gallstones. Gallstones are a serious but common side effect in people who take SOMATULINE DEPOT and have acromegaly and GEP-NET. Your healthcare provider may check your gallbladder before and during treatment with SOMATULINE DEPOT. Possible complications of gallstones include inflammation and infection of the gall bladder, and pancreatitis. Tell your healthcare provider if you get any symptoms of gallstones, including:

- sudden pain in your upper right stomach area (abdomen)
- yellowing of your skin and whites of your eyes
- nausea

- sudden pain in your right shoulder or between your shoulder blades
- fever with chills

- Fatty stool. SOMATULINE DEPOT may cause your body to have issues absorbing dietary fats. Tell your healthcare provider if you have any new or worsening symptoms including fatty stools, changes in the color of your stools, loose stools, stomach (abdominal) bloating or weight loss.
- Changes in your blood sugar (high blood sugar or low blood sugar). If you have diabetes, test your blood sugar as your healthcare provider tells you to. Your healthcare provider may change your dose of diabetes medicine especially when you first start receiving SOMATULINE DEPOT or if your dose of SOMATULINE DEPOT changes. High blood sugar is a common side effect in people with GEP-NET. Tell your healthcare provider right away if you have any signs or symptoms of high blood sugar or low blood sugar.
  Signs and symptoms of high blood sugar may include:

- increased thirst
- increased appetite
- nausea

- weakness or tiredness
- urinating more often than normal
- your breath smells like fruit

Signs and symptoms of low blood sugar may include:

- dizziness or lightheadedness
- sweating
- confusion
- headache

- blurred vision
- slurred speech
- shakiness

- fast heartbeat
- irritability or mood changes
- hunger

- Slow heart rate. Tell your healthcare provider right away if you have slowing of your heart rate or if you have symptoms of a slow heart rate, including:

- dizziness or lightheadedness
- fainting or near-fainting

- chest pain
- shortness of breath

- confusion or memory problems
- weakness, extreme tiredness

- High blood pressure. High blood pressure can happen in people who receive SOMATULINE DEPOT and is a common side effect in people with GEP-NET.
- Changes in thyroid function. SOMATULINE DEPOT can cause the thyroid gland to not make enough thyroid hormones that the body needs (hypothyroidism) in people who have acromegaly. Tell your healthcare provider if you have signs and symptoms of low thyroid hormones levels, including:

- fatigue
- weight gain
- a puffy face

- being cold all of the time
- constipation
- dry skin

- thinning, dry hair
- decreased sweating
- depression

The most common side effects of SOMATULINE DEPOT in people with acromegaly include:

- diarrhea
- stomach area (abdominal) pain

- nausea
- pain, itching, or a lump at the injection site

The most common side effects of SOMATULINE DEPOT in people with GEP-NET include:

- stomach area (abdominal) pain
- muscle and joint aches
- vomiting

- headache
- pain, itching, or a lump at the injection site

The most common side effects of SOMATULINE DEPOT in people with carcinoid syndrome include:

- headache

- dizziness

- muscle spasm

Tell your healthcare provider right away if you have signs of an allergic reaction after receiving SOMATULINE DEPOT, including:

- swelling of your face, lips, mouth or tongue
- breathing problems
- fainting, dizziness, feeling lightheaded (low blood pressure)
- itching

- flushing or redness of your skin
- rash
- hives

These are not all the possible side effects of SOMATULINE DEPOT. Call your doctor for medical advice about side effects. You may report side effects to FDA at 1-800-FDA-1088.

General information about the safe and effective use of SOMATULINE DEPOT.

Medicines are sometimes prescribed for purposes other than those listed in a Patient Information leaflet. Do not receive SOMATULINE DEPOT for a condition for which it was not prescribed. You can ask your healthcare provider for information about SOMATULINE DEPOT that is written for health professionals.

What are the ingredients in SOMATULINE DEPOT?

Active ingredient: lanreotide acetate

Inactive ingredients: water for injection and acetic acid (for pH adjustment)

Manufactured by: Ipsen Pharma Biotech, Parc d'Activities du Plateau de Signes, 83870 Signes, France

Manufactured for: Ipsen Biopharmaceuticals, Inc., 1 Main Street, Unit 700, Cambridge, MA 02142 USA.

For more information, go to www.somatulinedepot.com or call Ipsen Biopharmaceuticals, Inc. at 1-855-463-5127.

This Patient Information has been approved by the U.S. Food and Drug Administration.

Revised: 07/2024

INSTRUCTIONS FOR USE

Somatuline®Depot
(lanreotide) Injection

Instructions for Use – Page 1

IMPORTANT
If you have any questions about this medication or procedure, call 1-855-463-5127

Manufactured By:
Ipsen Pharma Biotech
83870 Signes France

Before You Begin Injection

1. Please read both sides of these Instructions for Use before using the device. FOLLOW THIS PROCEDURE EXACTLY, AS IT MAY DIFFER FROM YOUR PAST EXPERIENCE.
2. Somatuline Depot should be administered by a Healthcare Professional.
3. If this device is dropped or damaged in any way, please call 1-855-463-5127
A. Storage of Somatuline Depot
  When you receive the medication, follow these steps for storing Somatuline Depot.
  Important: Somatuline Depot MUST BE REFRIGERATED. DO NOT ALLOW IT TO REACH ROOM TEMPERATURE UNTIL READY TO USE.
  A1. Remove box from cold pack. Do not open box.
  A2. Check the following:
    Note: Call 1-855-463-5127 if you have any questions.
  A3. Place unopened box in your refrigerator.
    DO NOT PLACE IN FREEZER.

B. Prepare to Inject
  B1. Confirm that date of this injection is as prescribed.
  B2. Remove box from refrigerator. Open box and remove contents.
  B3. Confirm that pouch is sealed and not damaged.
  B4. Check that the dose is as prescribed and the expiration date has not passed.
  B5. Let pouch sit for 30 MINUTES to reach room temperature. DO NOT OPEN the pouch until ready to inject.
    - Injection of cold medication may be painful.
    Note: Product left in its sealed pouch at room temperature (not to exceed 104° F or 40 °C) for up to 72 hours may be returned to the refrigerator for continued storage and use at a later time.
  B6. Find a clean, comfortable area for the patient to relax during procedure.
    - It's important that the patient remains as still as possible during the injection.
    OR
  B7. The person administering the injection must wash his/her hands with soap and water.
    Follow the doctor or institution's policy on the use of surgical gloves during this procedure.
  B8. Tear open pouch along dotted line starting at the notch.
  B9. Do the following:
    1. Prior to administration, inspect the SOMATULINE DEPOT syringe visually for particulate matter and discoloration. Do not administer if particulate matter or discoloration is observed. The content of the prefilled syringe is a semi-solid phase having a gel-like appearance, with viscous characteristics and a color varying from white to pale yellow. The supersaturated solution can also contain micro bubbles that can clear up during injection. These differences are normal and do not interfere with the quality of the product.
    2. Confirm that expiration date on the device has not passed.
    3. Make sure it is the right dosage:
      - 60 mg, or
      - 90 mg, or
      - 120 mg
    4. Set device aside on the empty pouch.
    Note: Call 1-855-463-5127if you have any questions.
  B10. Choose which side of the buttocks to inject.
    1. Switch sides with each injection.
    2. Avoid areas with moles, scar tissue, reddened skin, or skin that feels bumpy.
    3. Only inject in the areas market with OK in the picture.
    Important: It is very important that you only inject in one of the areas marked OK in the picture (upper outer quadrants of the right or left buttocks).
  B11. Clean area to be injected.

Turn page over for additional instructions

Somatuline®Depot
(lanreotide) Injection

Instructions for Use- Page 2

IMPORTANT
If you have any questions about this medication or procedure, call 1-855-463-5127.

Ipsen Pharma Biotech
83870 Signes France

C. Inject
  Important: This is a single-use pre-filled syringe with a retractable needle.
  - ALL the medication must be injected during this use.
  - If you drop or damage this device in any way, please call 1-855-463-5127
  Follow these injection instructions exactly! This procedure may be different from your past experience.
  C1. BEFORE injecting,
    REMOVE the pre-filled syringe from its tray.
    Discard tray.
  C2. REMOVE NEEDLE CAP
    - HOLD PRE-FILLED SYRINGE BY THE SYRINGE BODY and PULL OFF the needle cap to remove it.
    - DO NOT HOLD the pre-filled syringe by the plunger
    - Discard needle cap.
  C3. Hold pre-filled syringe by the syringe body. The pre-filled syringe is now ready for injection.
  C4. FLATTEN injection area using the thumb and index finger of your other hand to stretch the skin.
    - Do NOT pinch skin.
  C5. Insert needle PERPENDICULAR to the skin (90 degree angle).
    - Use a strong, straight, dart-like motion to quickly INSERT THE NEEDLE ALL THE WAY INTO THE SKIN.
    - It is very important that you insert the needle COMPLETELY. You should not see any needle once it is fully inserted.
    - Do not aspirate (do not draw back).
    1. Do not insert needle at an acute angle.
    2. Make sure needle is fully inserted.
  C6. When needle is completely inserted, release injection site that has been flattened by your hand.
  C7. Push plunger with STEADY, VERY FIRM PRESSURE.
    - The medication is thicker and harder to push than you might expect.
    - While depressing plunger, slowly count to 20 and CONTINUE STEADY PRESSURE on the plunger. You may find it helpful to say:
      a. "1 one-thousand"
      b. "2 one-thousand"
      c. "3 one-thousand" up to "20 one-thousand"
    Note: Pushing the plunger too fast may cause discomfort to the patient or may break device.
  C8. GIVE PLUNGER A FINAL PUSH to make sure you cannot depress the plunger further.
    Continue steady pressure with your thumb.
  C9. While continuing to hold down the plunger, remove the needle from the injection site (1), then allow the needle to retract by removing your thumb from the plunger (2) (3).
    - If needle does not retract, push plunger again to engage safety mechanism. The needle will then retract.
  C10. If needed, gently apply gauze pad to injection area.
    - Important: NEVER RUB OR MASSAGE the injection site.
D. Dispose of Pre-filled Syringe
  D1. Discard used device into a hard plastic container with a screw top (such as a detergent bottle) or sharps container as per your institutional policy.
  D2. Wash your hands.

PRINCIPAL DISPLAY PANEL - 60 mg/0.2 mL Syringe Carton - NDC 15054-1060-4

Rx only

Somatuline® Depot
(lanreotide) Injection
60 mg/0.2 mL

NDC 15054 1060 4

For deep subcutaneous injection

For single use only. Discard unused portion.
Somatuline® Depot should be administered by a healthcare professional.

Leave at room temperature for 30 minutes before administration.

CONTENTS: This box contains one (1) pre-filled syringe.

60 mg/0.2 mL

IPSEN

PRINCIPAL DISPLAY PANEL - 90 mg/0.3 mL Syringe Carton - NDC 15054-1090-4

Rx only

Somatuline® Depot
(lanreotide) Injection
90 mg/0.3 mL

NDC 15054 1090 4

For deep subcutaneous injection

For single use only. Discard unused portion.
Somatuline® Depot should be administered by a healthcare professional.

Leave at room temperature for 30 minutes before administration.

CONTENTS: This box contains one (1) pre-filled syringe.

90 mg/0.3 mL

IPSEN

PRINCIPAL DISPLAY PANEL - 120 mg/0.5 mL Syringe Carton - NDC 15054-1120-4

Rx only

Somatuline® Depot
(lanreotide) Injection
120 mg/0.5 mL

NDC 15054 1120 4

For deep subcutaneous injection

For single use only. Discard unused portion.
Somatuline® Depot should be administered by a healthcare professional.

Leave at room temperature for 30 minutes before administration.

CONTENTS: This box contains one (1) pre-filled syringe.

120 mg/0.5 mL

IPSEN